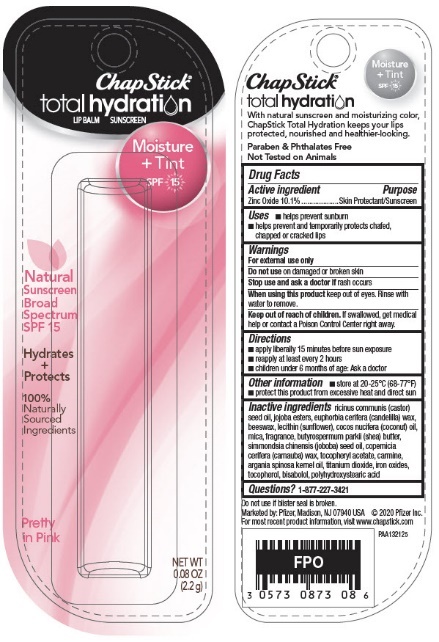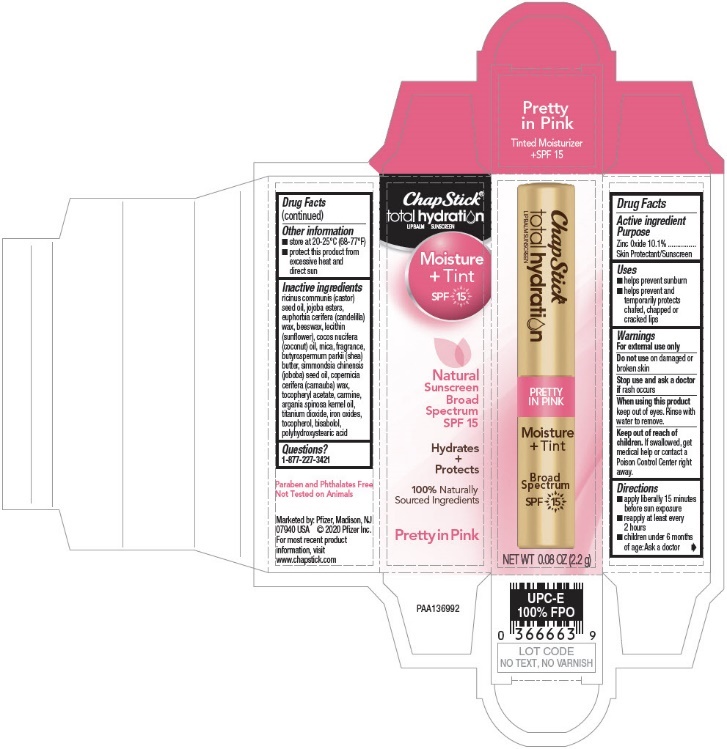 DRUG LABEL: Chapstick Total Hydration Moisture Tint Pretty in Pink
NDC: 0573-0873 | Form: STICK
Manufacturer: Haleon US Holdings LLC
Category: otc | Type: HUMAN OTC DRUG LABEL
Date: 20240322

ACTIVE INGREDIENTS: ZINC OXIDE 101 mg/1 g
INACTIVE INGREDIENTS: CASTOR OIL; HYDROGENATED JOJOBA OIL/JOJOBA OIL, RANDOMIZED (IODINE VALUE 57-61); HYDROGENATED JOJOBA OIL/JOJOBA OIL, RANDOMIZED (IODINE VALUE 40-44); CANDELILLA WAX; YELLOW WAX; LECITHIN, SUNFLOWER; COCONUT OIL; MICA; SHEA BUTTER; JOJOBA OIL; CARNAUBA WAX; .ALPHA.-TOCOPHEROL ACETATE; CARMINIC ACID; ARGAN OIL; TITANIUM DIOXIDE; FERRIC OXIDE RED; TOCOPHEROL; LEVOMENOL; POLYHYDROXYSTEARIC ACID (2300 MW)

Drug Facts

Active ingredient

Zinc Oxide 10.1%

Purpose

Skin Protectant/Sunscreen

Uses

- helps prevent sunburn
- helps prevent and temporarily protects chafed, chapped or cracked lips

Warnings

For external use only

Do not use on damaged or broken skin

Stop use and ask a doctor if rash occurs

When using this product keep out of eyes. Rinse with water to remove.

Keep out of reach of children. If swallowed, get medical help or contact a Poison Control Center right away.

Directions

- apply liberally 15 minutes before sun exposure
- reapply at least every 2 hours
- children under 6 months of age: Ask a doctor

Other information

- store at 20-25°C (68-77°F)
- protect this product from excessive heat and direct sun

Inactive ingredients

ricinus communis (castor) seed oil, jojoba esters, euphorbia cerifera (candelilla) wax, beeswax, lecithin (sunflower), cocos nucifera (coconut) oil, mica, fragrance, butyrospermum parkii (shea) butter, simmondsia chinensis (joboba) seed oil, copernicia cerifera (carnauba) wax, tocopheryl acetate, carmine, argania spinosa kernel oil, titanium dioxide, iron oxides, tocopherol, bisabolol, polyhydroxystearic acid

Questions?

1-877-227-3421

PRINCIPAL DISPLAY PANEL - 2.2 g Cylinder Blister Pack

ChapStick®
total hydration
LIP BALM
SUNSCREEN

Moisture
+ Tint
SPF 15

Natural
Sunscreen
Broad
Spectrum
SPF 15

Hydrates
+
Protects

100%
Naturally
Sourced
Ingredients

Pretty
in Pink

NET WT
0.08 OZ
(2.2 g)

PRINCIPAL DISPLAY PANEL - 2.2 g Cylinder Carton

ChapStick®
total hydration
LIP BALM SUNSCREEN

PRETTY
IN PINK

Moisture
+ Tint

Broad
Spectrum
SPF 15

NET WT 0.08 OZ (2.2 g)